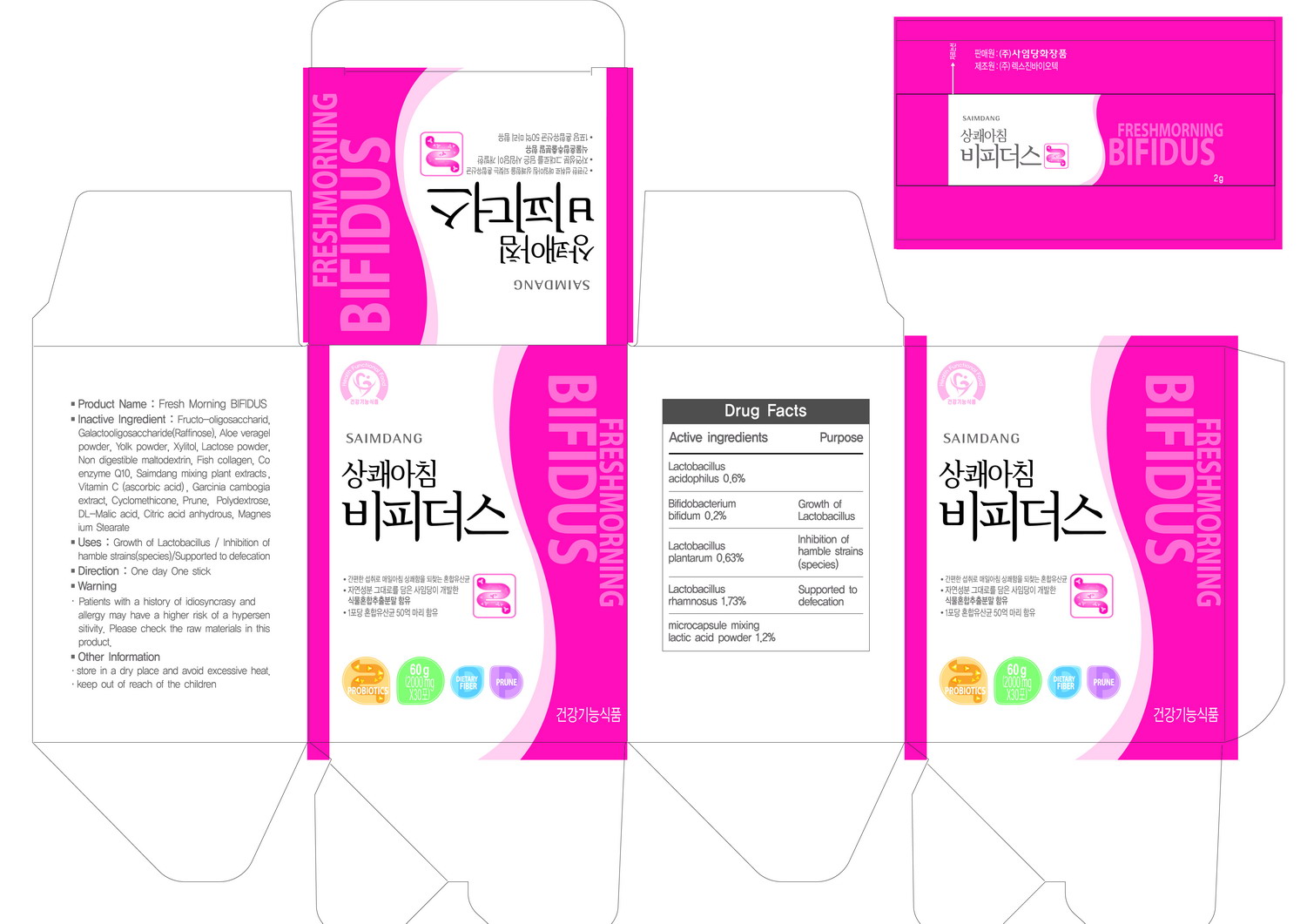 DRUG LABEL: Fresh Morning Bifidus
NDC: 51220-1001 | Form: POWDER
Manufacturer: Saimdang Cosmetics Co., Ltd
Category: otc | Type: HUMAN OTC DRUG LABEL
Date: 20100821

ACTIVE INGREDIENTS: LACTIC ACID 0.0316 mg/1 mg

Drug Facts

ACTIVE INGREDIENT

Active ingredients: Lactobacillus acidophilus, Bifidobacterium bifidum, Lactobacillus plantarum, Lactobacillus rhamnosus, microcapsule mixing lactic acid powder

DESCRIPTION

• Product Name : Fresh Morning BIFIDUS
• Inactive Ingredient: Fructo-oligosaccharid,
Galactooligosaccharide(Raffinose), Aloe veragel
powder, Yolk powder, Xylitol, Lactose powder,
Non digestible maltodextrin, Fish collagen, Co
enzyme 010, Saimdang mixing plant extracts,
Vitamin C (ascorbic acid), Garcinia cambogia
extract, Cyclomethicone, Prune, Polydextrose,
DL-Malic acid, Citric acid anhydrous, Magnes
ium Stearate
• Uses : Growth of Lactobacillus / Inhibition of
hamble strains(species)/Supporled to defecation
• Direction : One day One stick
• Warning: . Patients with a history of idiosyncrasy and
allergy may have a higher risk of a hypersen
sitivity, Please check the raw materials in this
product
• Other Information
, store in a dry place and avoid excessive heat.
. keep out of reach of the children